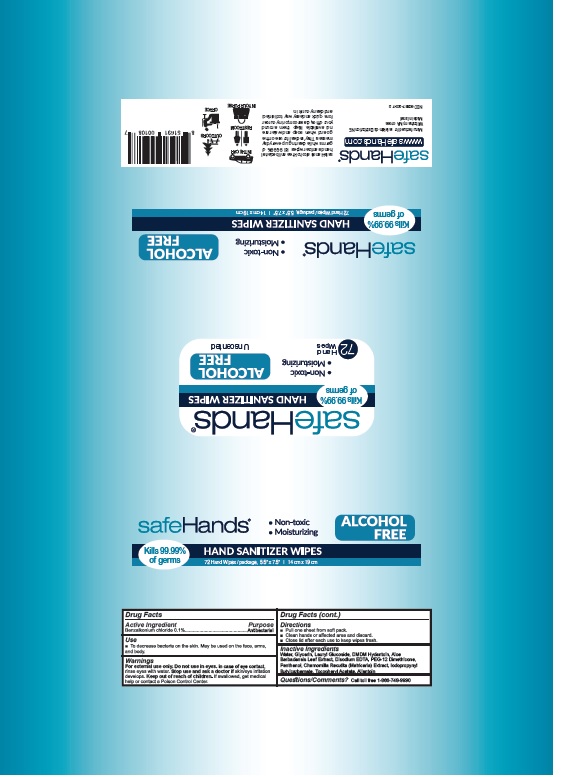 DRUG LABEL: safeHands Hand Sanitizer Wipes
NDC: 60867-200 | Form: CLOTH
Manufacturer: Safehands Distribution Ne, LLC
Category: otc | Type: HUMAN OTC DRUG LABEL
Date: 20211125

ACTIVE INGREDIENTS: BENZALKONIUM CHLORIDE 0.1 g/100 1
INACTIVE INGREDIENTS: WATER; GLYCERIN; LAURYL GLUCOSIDE; DMDM HYDANTOIN; ALOE VERA LEAF; EDETATE DISODIUM ANHYDROUS; PEG-12 DIMETHICONE; PANTHENOL; MATRICARIA CHAMOMILLA WHOLE; IODOPROPYNYL BUTYLCARBAMATE; .ALPHA.-TOCOPHEROL ACETATE; ALLANTOIN

safeHands Hand Sanitizer Wipes

Active Ingredient

Benzalkonium chloride 0.1%

Purpose

Antibacterial

Uses

• To decrease bacteria on the skin. May be used on the face, arms,

and body.

Warnings

For external use only.

Do not use in eyes.

In case of contact, rinse eyes thoroughly with water.

Stop use and ask a doctor if

skin/eye irritation develops.

Keep out of reach of children.

If swallowed, get medical help or contact a Poison Control Center.

Directions

• Pull one sheet from soft pack.

• Clean hands or affected area and discard.

• Close lid after each use to keep wipes fresh.

Inactive Ingredients

Water, Glycerin, Lauryl Glucoside, DMDM Hydantoin, Aloe
Barbadensis Leaf Extract, Disodium EDTA, PEG-12 Dimethicone,
Panthenol, Chamomilla Recutita (Matricaria) Extract, Iodopropynyl
Butylcarbamate, Tocopheryl Acetate, Allantoin

Questions/Comments?

Call toll free 1-866-748-9990

Package Labeling

SafeHands®

- Non-toxic
- Moisturizing

ALCOHOL FREE

HAND SANITIZEER WIPES

Kills 99.9% of germs

72 Hand Wipes / package, 5.5” x 7.5” | 14 cm x 19 cm

Manufactured for safeHands Distribution NE
Wilbraham, MA 01095
Made in Israel

NDC 60867-200-72

RES